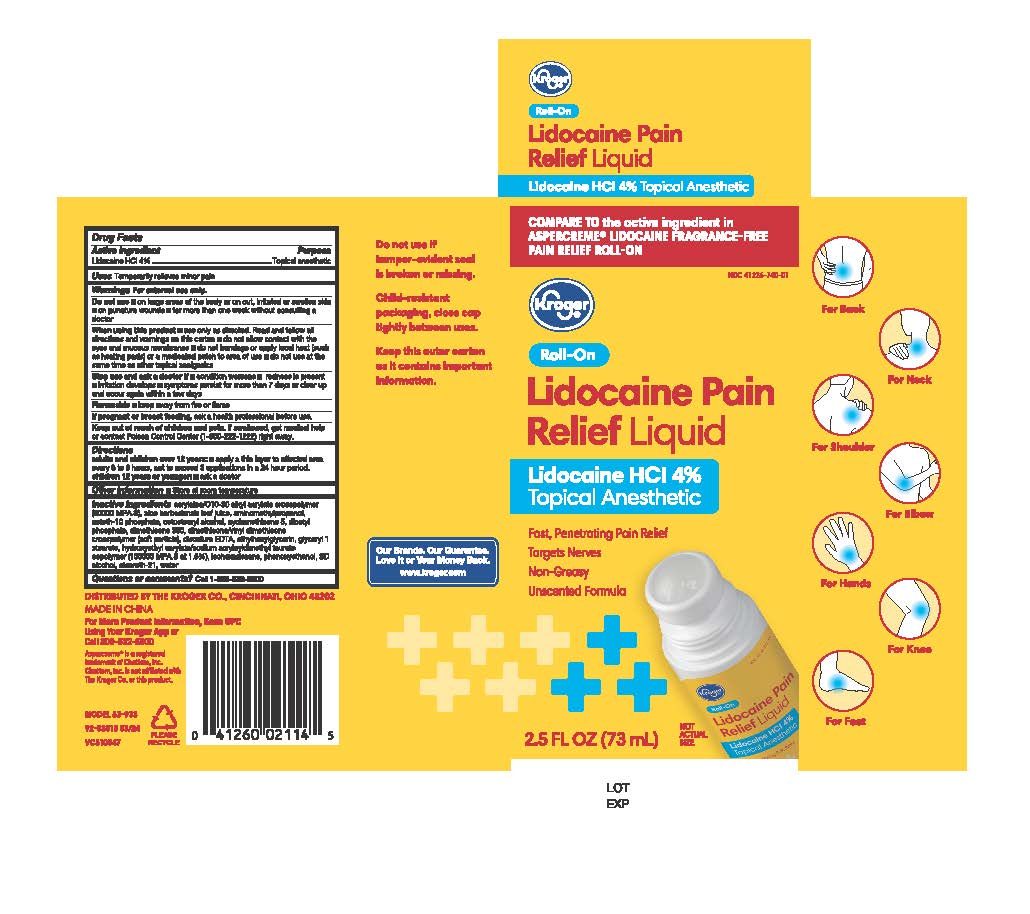 DRUG LABEL: Kroger Lidocaine Pain Relieving
NDC: 41226-740 | Form: LIQUID
Manufacturer: Kroger Company
Category: otc | Type: HUMAN OTC DRUG LABEL
Date: 20251228

ACTIVE INGREDIENTS: LIDOCAINE 4 g/1 mL
INACTIVE INGREDIENTS: DIMETHICONE/VINYL DIMETHICONE CROSSPOLYMER (SOFT PARTICLE); EDETATE DISODIUM ANHYDROUS; ACRYLATES/C10-30 ALKYL ACRYLATE CROSSPOLYMER (60000 MPA.S); GLYCERYL 1-STEARATE; DIMETHICONE 350; ETHYLHEXYLGLYCERIN; PHENOXYETHANOL; ALCOHOL; ALOE VERA LEAF; STEARETH-21; ISOHEXADECANE; HYDROXYETHYL ACRYLATE/SODIUM ACRYLOYLDIMETHYL TAURATE COPOLYMER (45000 MPA.S AT 1%); CYCLOMETHICONE 5; CETOSTEARYL ALCOHOL; AMINOMETHYLPROPANOL; DIHEXADECYL PHOSPHATE; CETETH-10 PHOSPHATE; WATER

Kroger Lidocaine Pain Relieving Roll-On

Active Ingredient

Lidocaine HCL 4%

Purpose

Topical anesthetic

Uses

Temporarily relieves minor pain

Warnings

For external use only

Do not use

On large areas of the body or on cut, irritated or swollen skin
■ on puncture wounds

■for more than one week without consulting a doctor

When using this product

■use only as directed. Read and follow all directions and warnings on this carton

■do not allow contact with the eyes and mucous membranes

■ do not bandage or apply local heat (such as heating pads) or a medicated patch to area of use

■do not use at the same time as other topical analgesics

Stop use and ask a doctor if

■ condition worsens ■ redness is present
■irritation develops

■symptoms persist for more than 7 days or clear up and occur again within a few days

If pregnant or breastfeeding

ask a health professional before use

Keep out of reach of children and pets

If swallowed, get medical help or contact Poison Control Center (1-800-222-1222) right away.

Directions

adults and children over 12 years: ■apply a thin layer to affected area every 6 to 8 hours, not to exceed 3 applications in a 24 hour period.

children 12 years or younger: ■ask a doctor

Other information

Store at room temperature

Inactive Ingredients

acrylates/C10-30 alkyl acrylate crosspolymer (60000 MPA.S), aloe barbadensis leaf juice, am nomethylpropanol, ceteth-10 phosphate, cetostearyl alcohol, cyclomethicone 5, dicetyl phosphate, dimethicone 350, dimethicone/vinyl dimethicone crosspolymer (soft particle),
disodium EDTA, ethylhexylglycerin, glyceryl 1 stearate, hydroxyethyl acrylate/sodium acryloyld methyl taurate copolymer (100000 MPA.S at 1.5%), sohexadecane, phenoxyethanol, SD alcohol, steareth-21, water

Questions or Comments

Call 1-800-632-6900